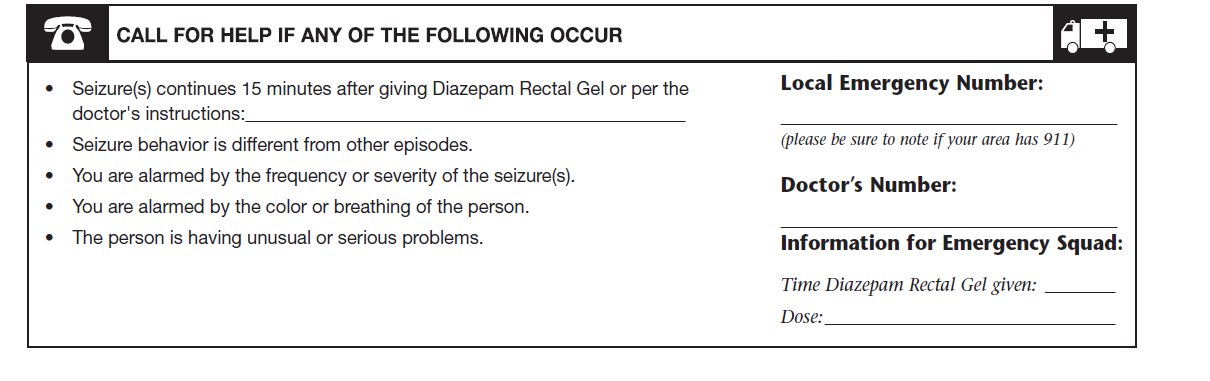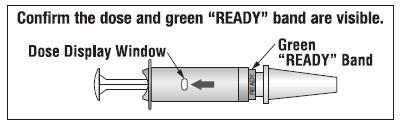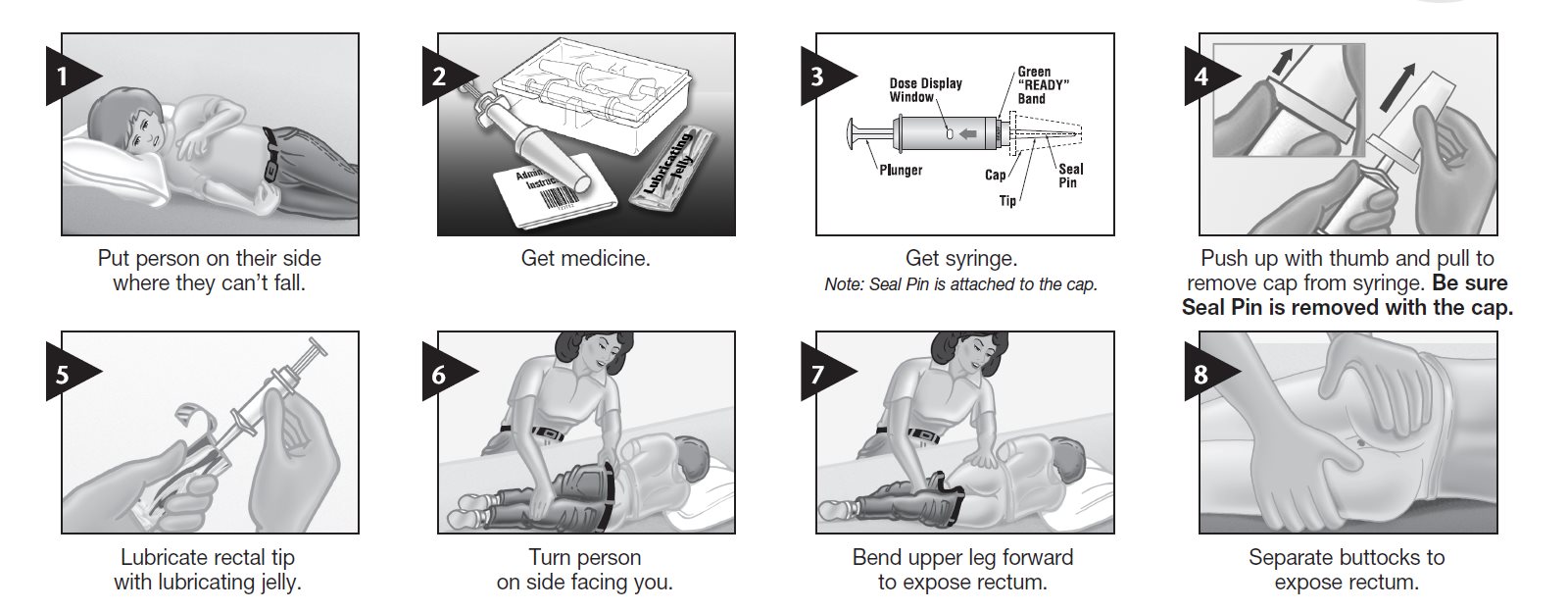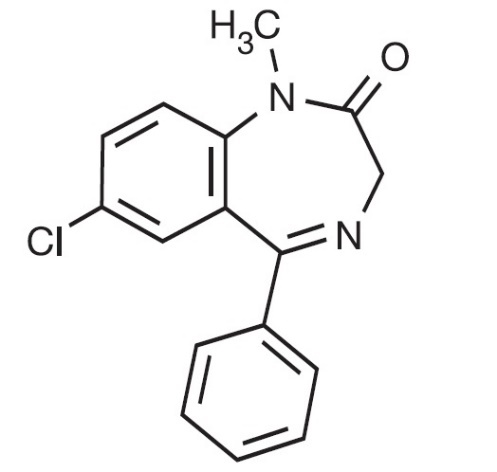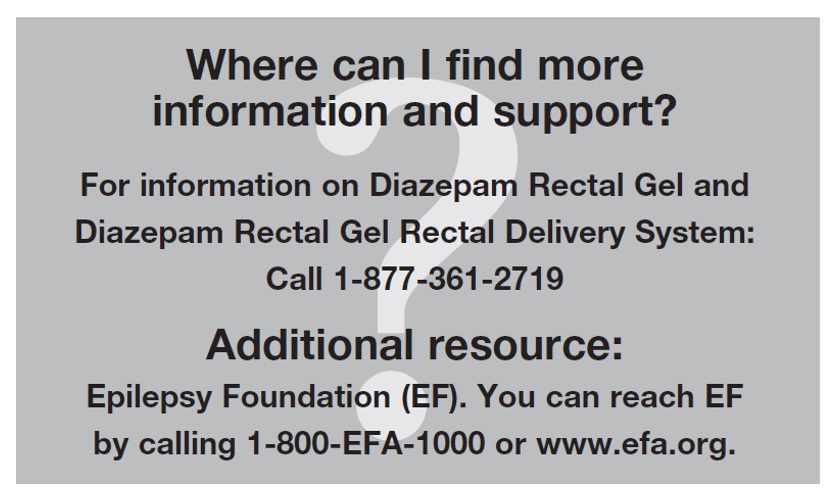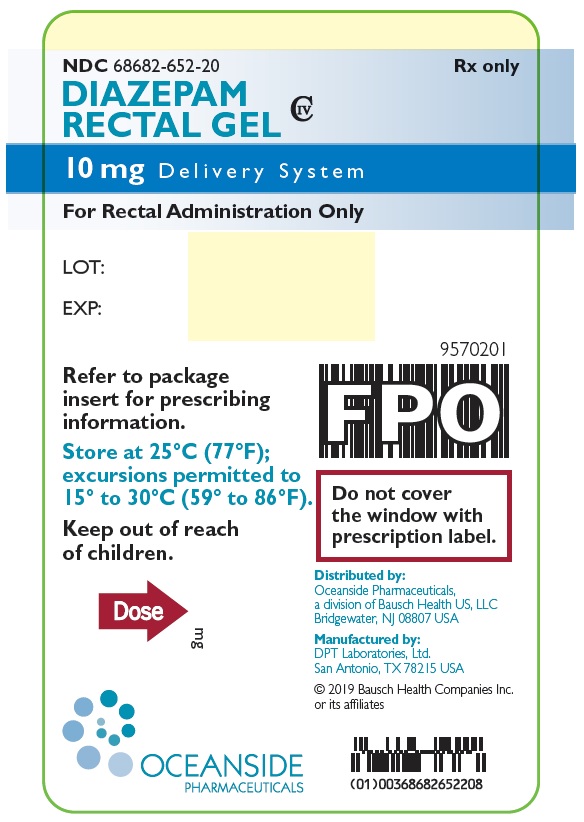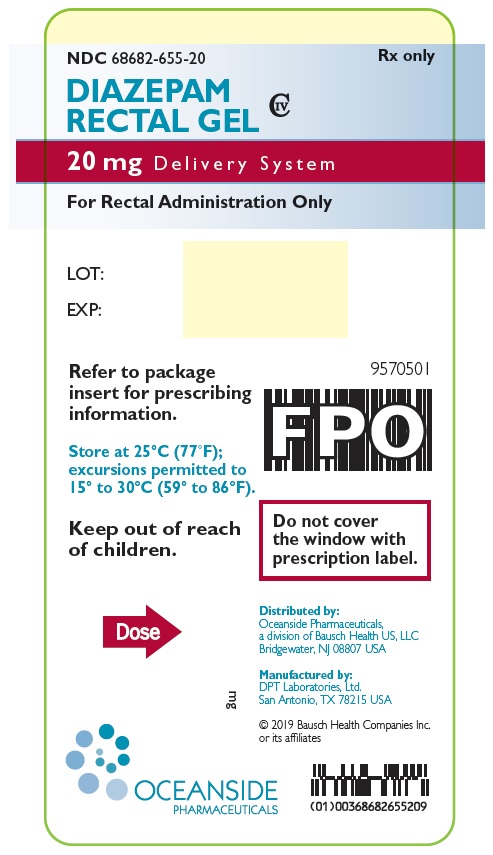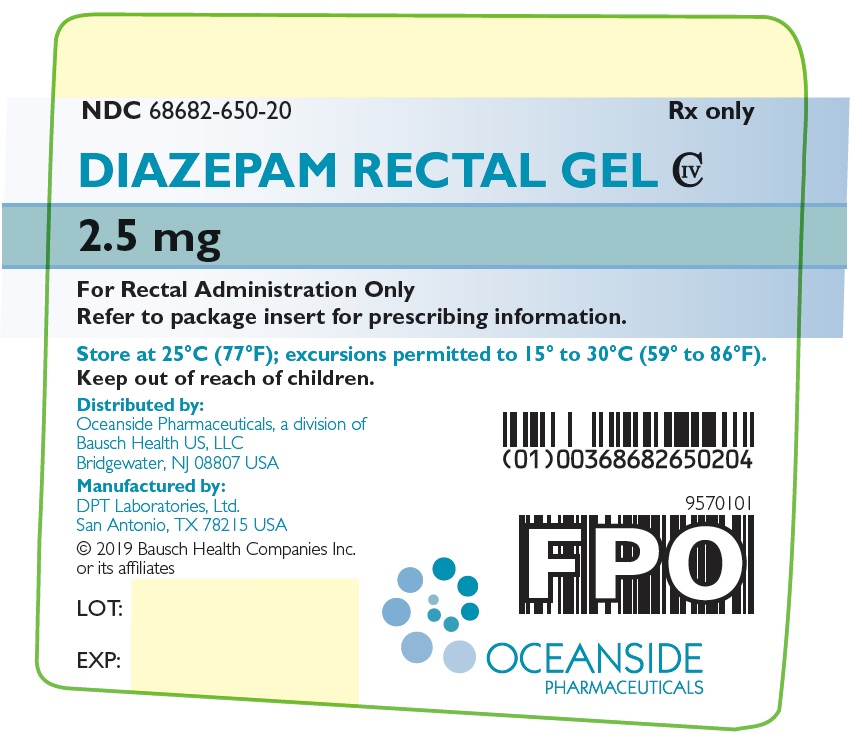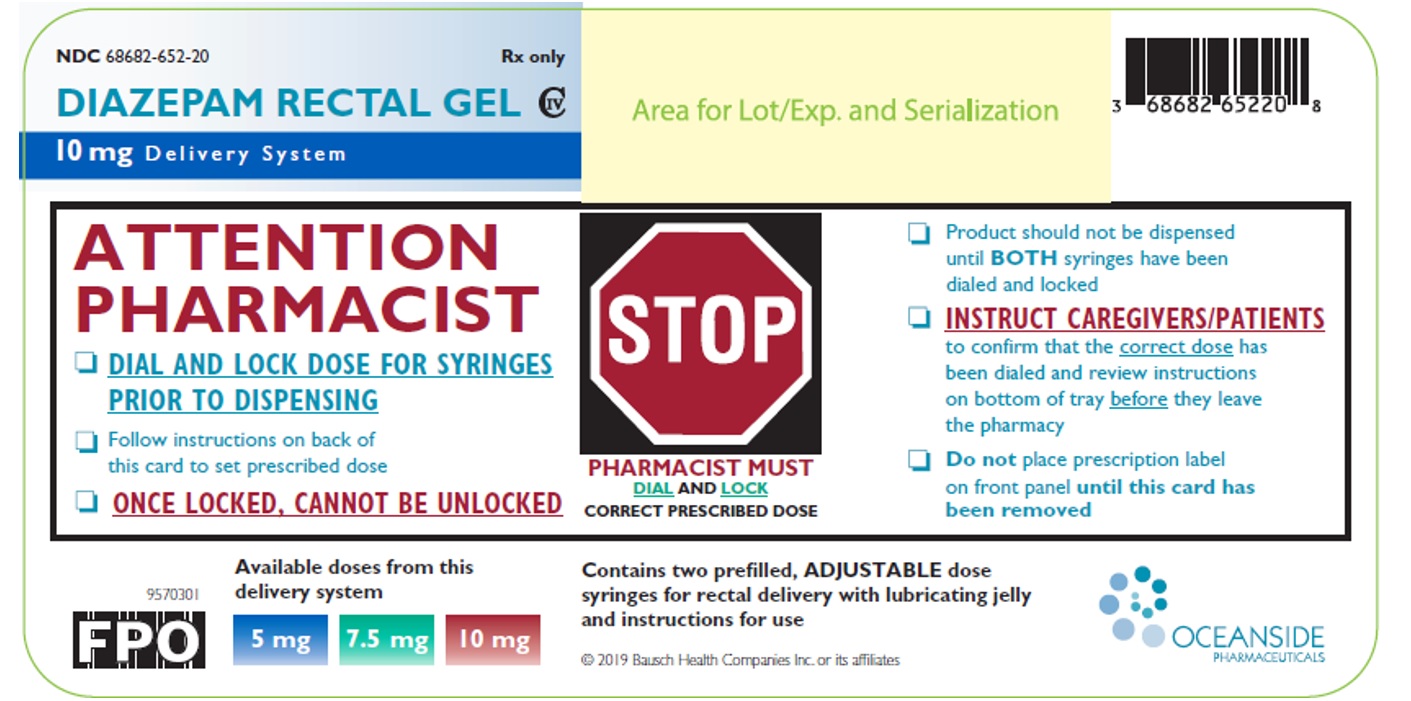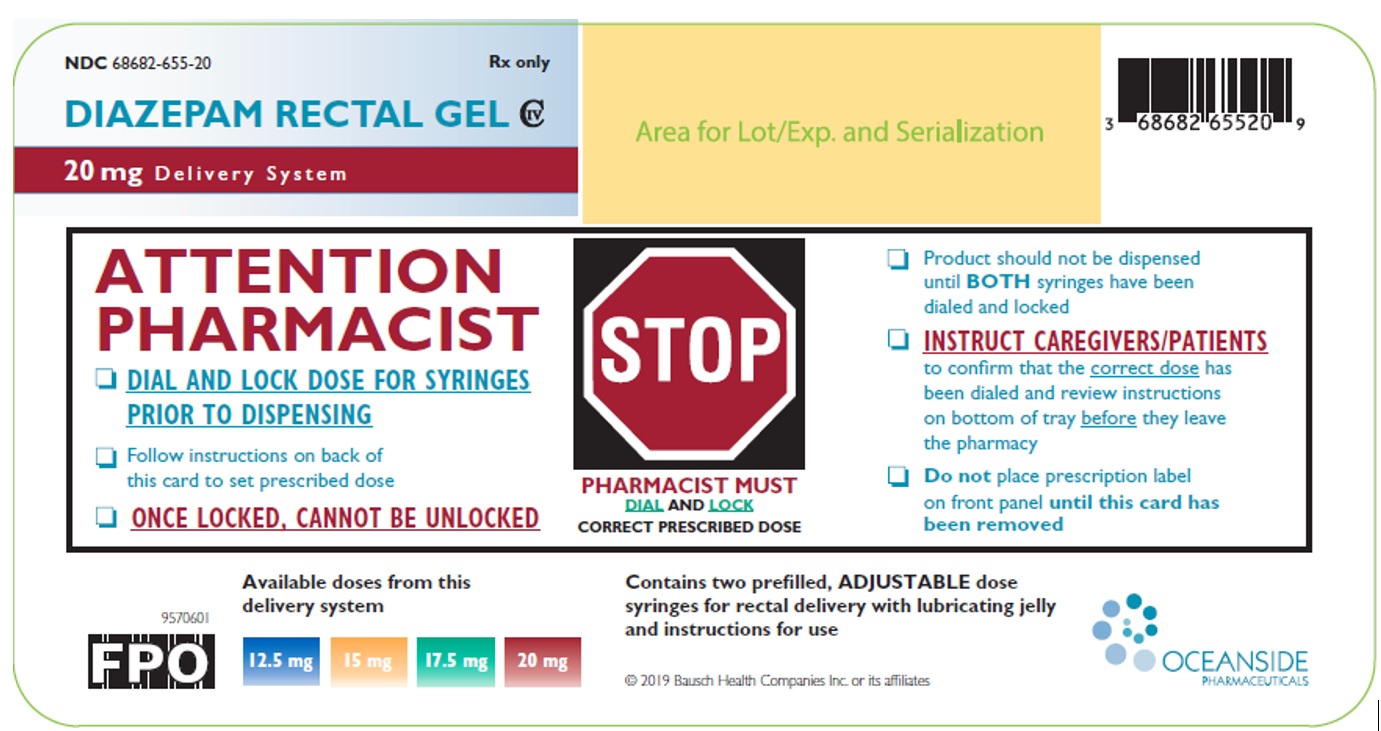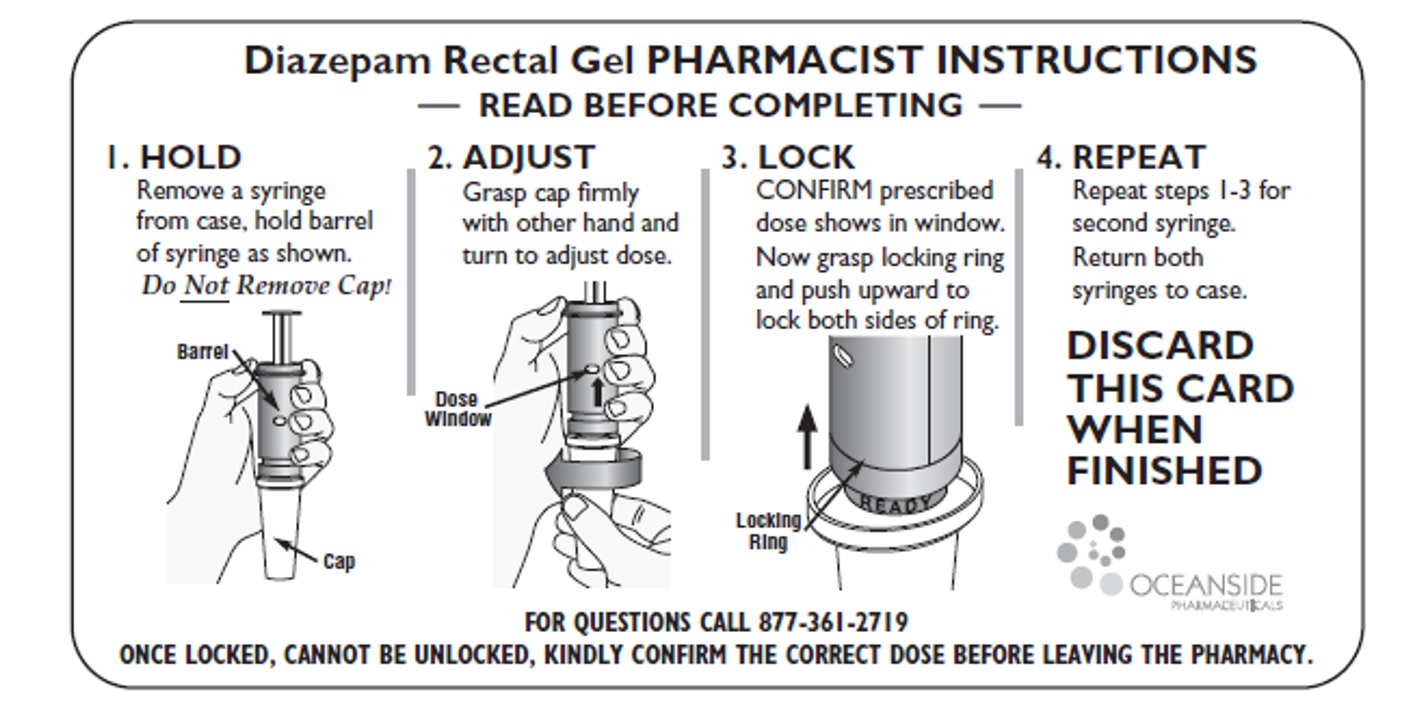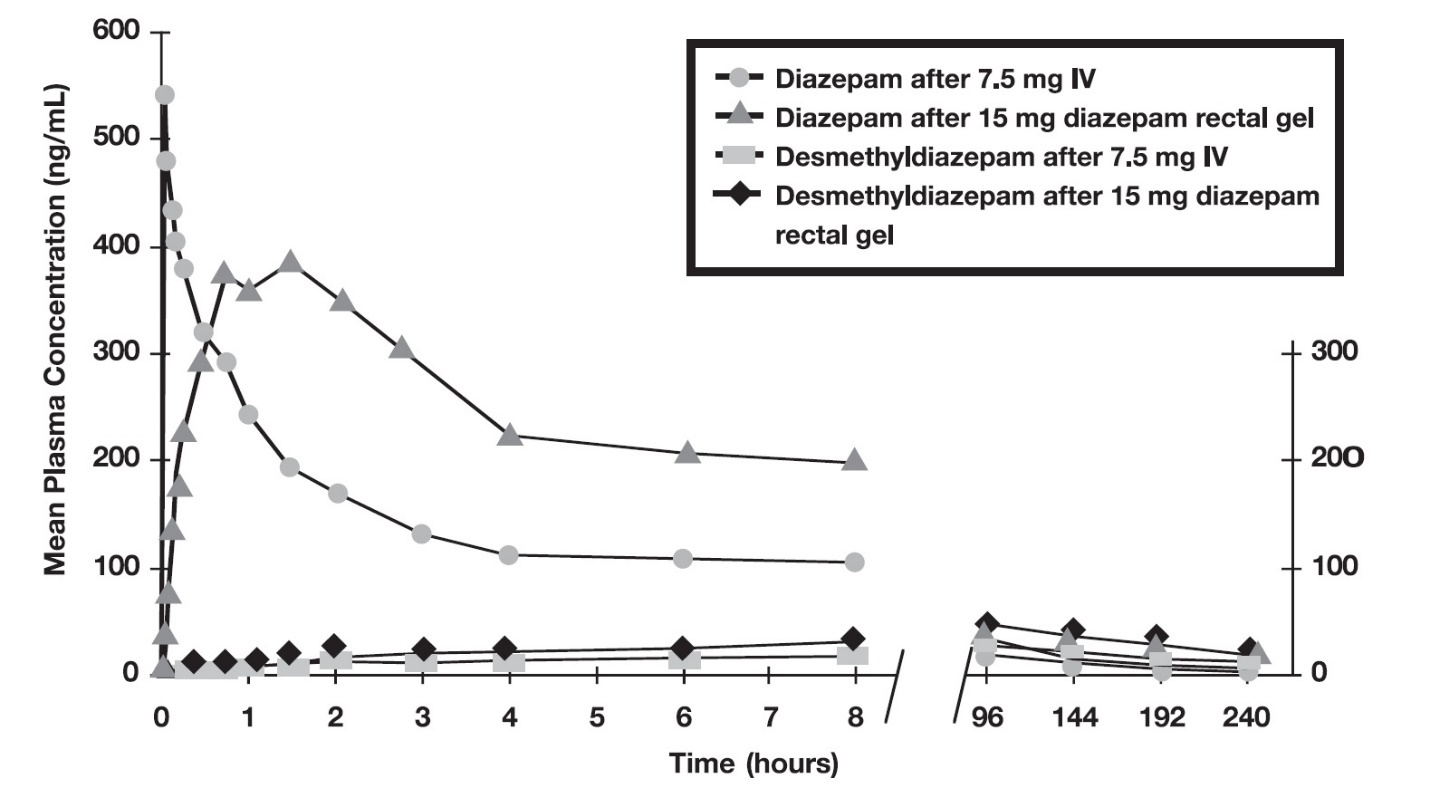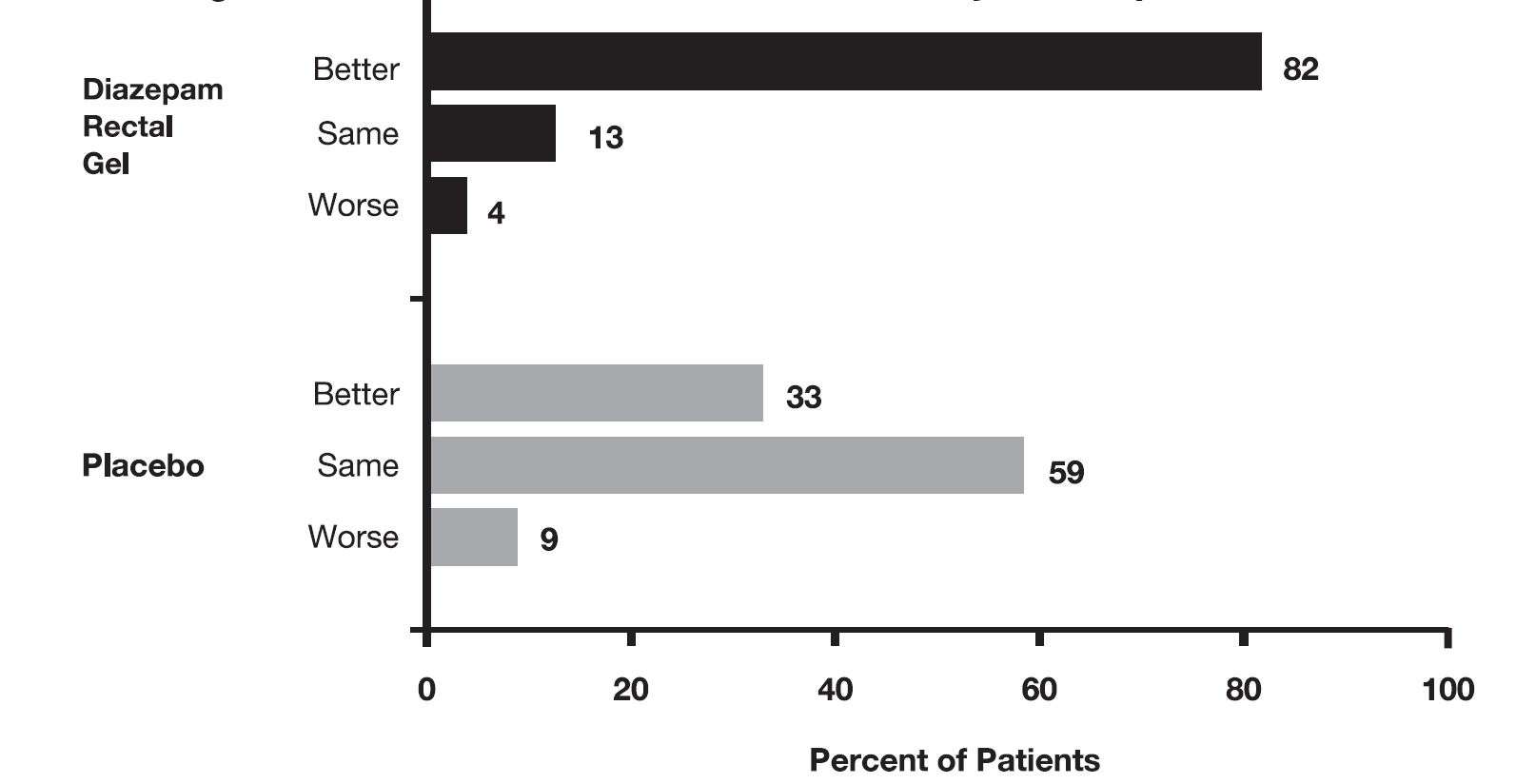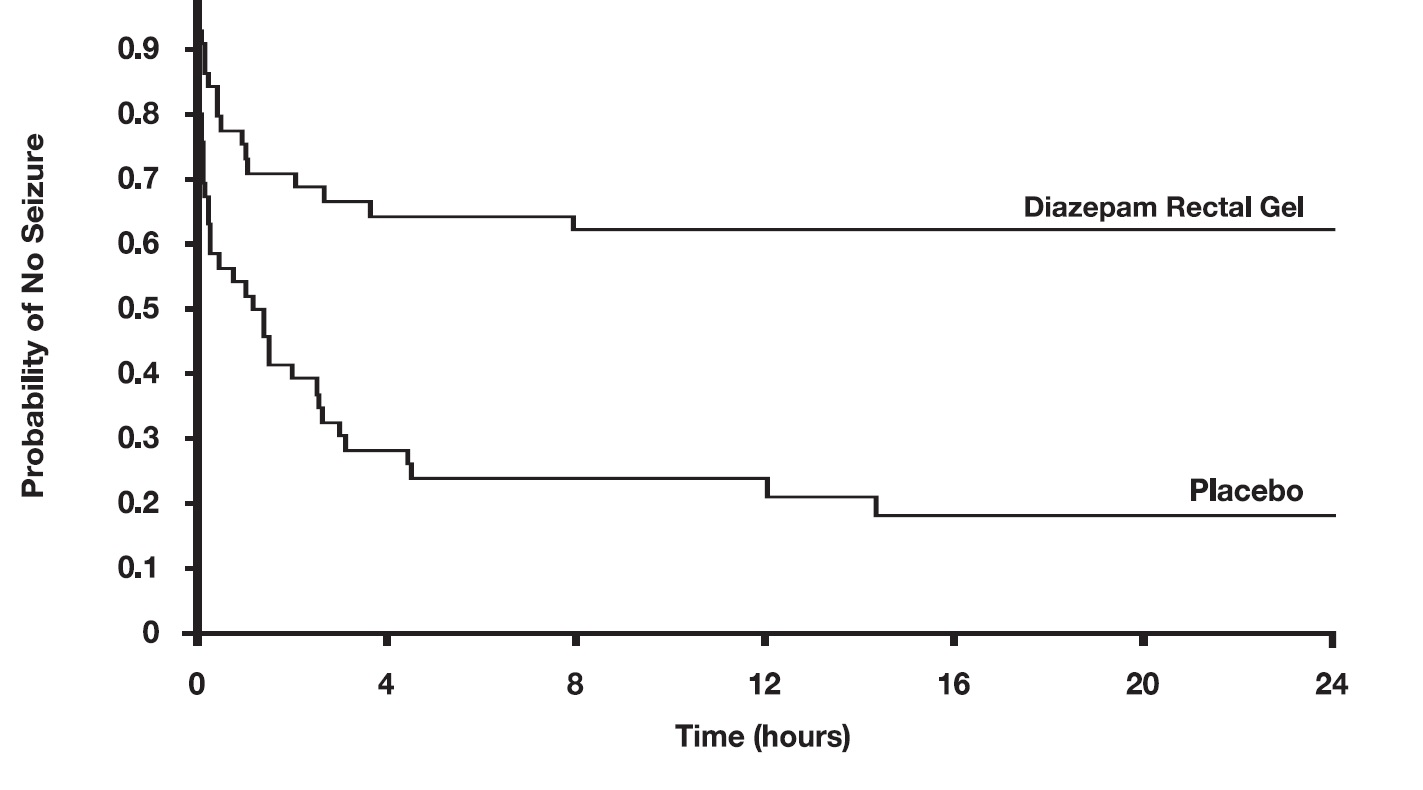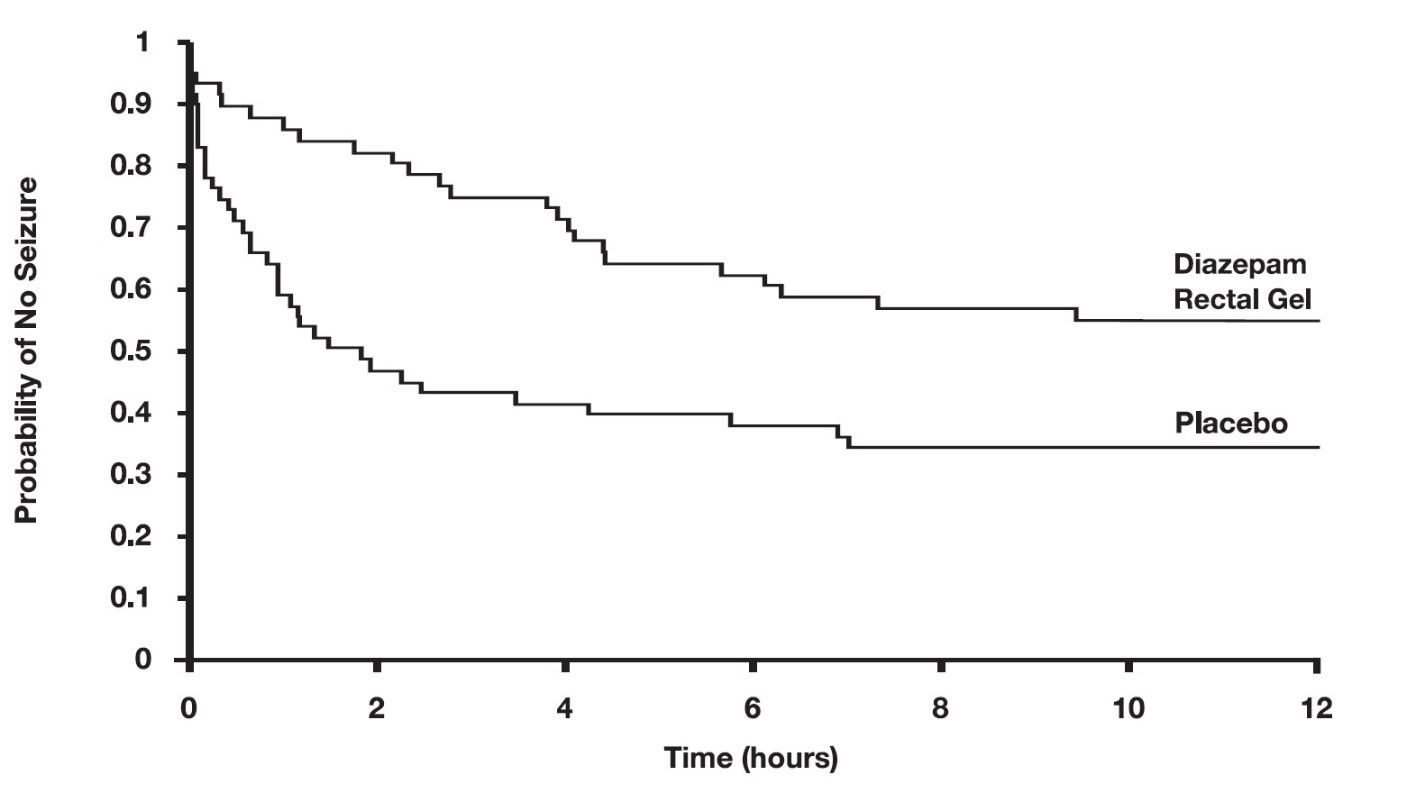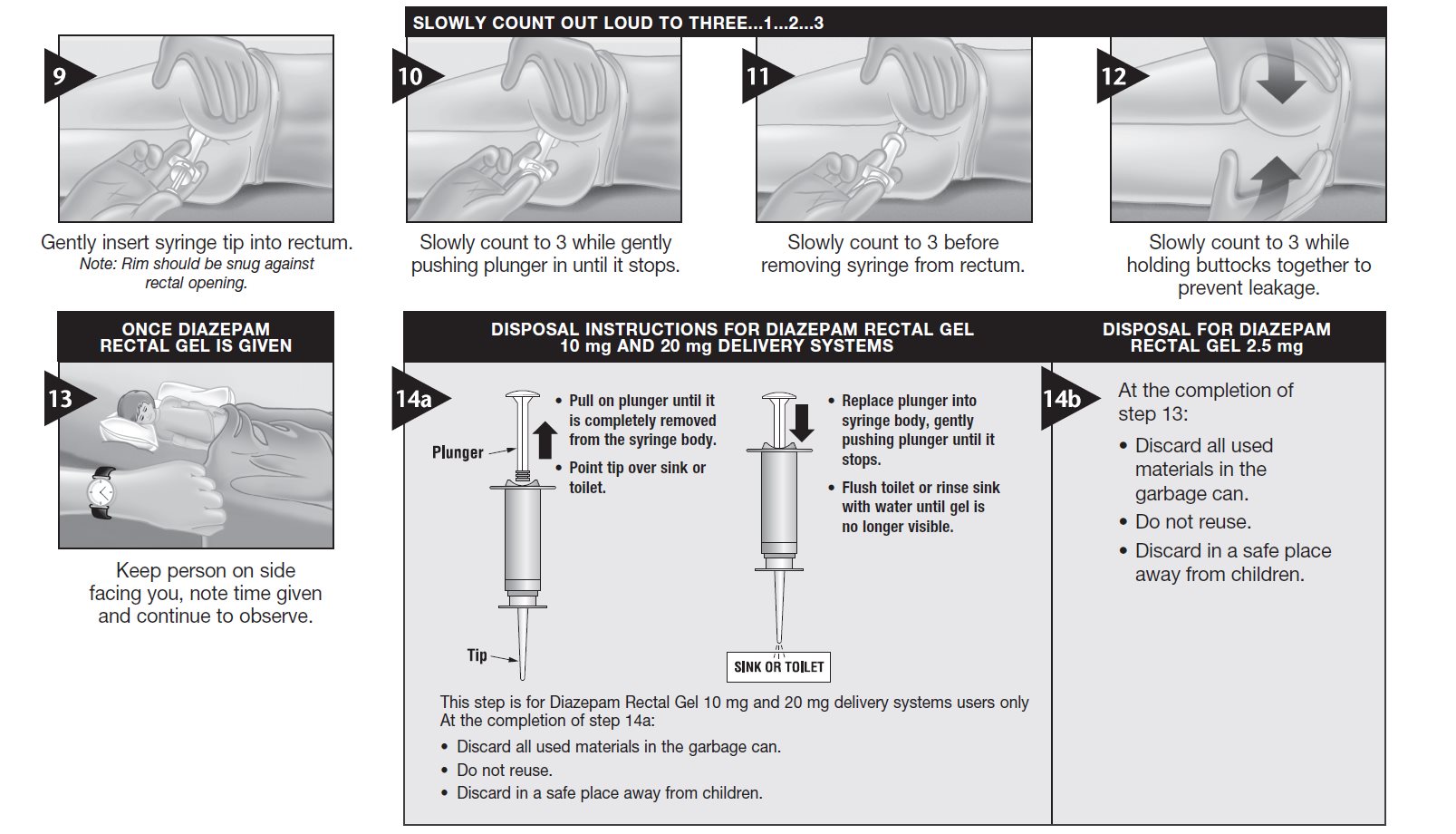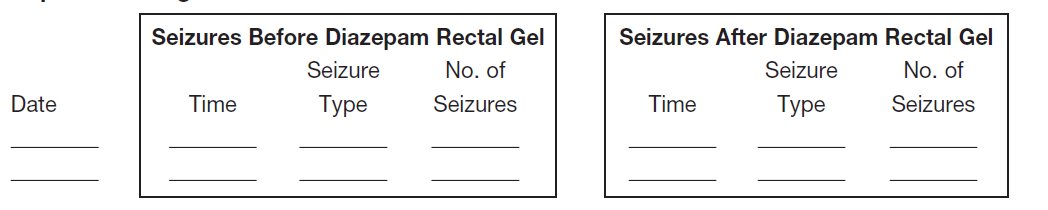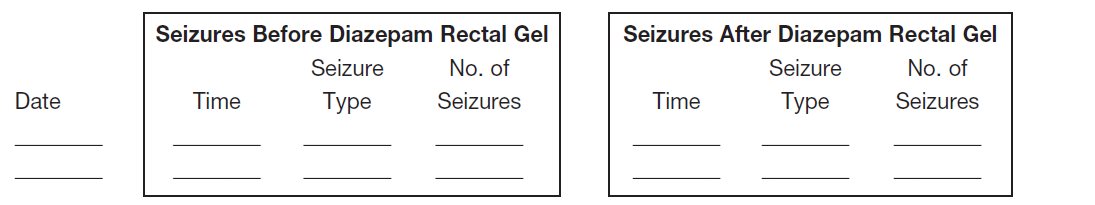 DRUG LABEL: Diazepam
NDC: 68682-652 | Form: GEL
Manufacturer: Oceanside Pharmaceuticals
Category: prescription | Type: HUMAN PRESCRIPTION DRUG LABEL
Date: 20240104
DEA Schedule: CIV

ACTIVE INGREDIENTS: DIAZEPAM 10 mg/2 mL
INACTIVE INGREDIENTS: PROPYLENE GLYCOL; ALCOHOL; HYPROMELLOSE, UNSPECIFIED; SODIUM BENZOATE; BENZYL ALCOHOL; BENZOIC ACID; WATER

Diazepam Rectal Gel C-IV
Rectal Delivery System

WARNING: RISKS FROM CONCOMITANT USE WITH OPIOIDS; ABUSE, MISUSE, AND ADDICTION; and DEPENDENCE AND WITHDRAWAL REACTIONS

- Concomitant use of benzodiazepines and opioids may result in profound sedation, respiratory depression, coma, and death. Reserve concomitant prescribing of these drugs for patients for whom alternative treatment options are inadequate. Limit dosages and durations to the minimum required. Follow patients for signs and symptoms of respiratory depression and sedation (see WARNINGSand PRECAUTIONS).
- The use of benzodiazepines, including diazepam rectal gel, exposes users to risks of abuse, misuse, and addiction, which can lead to overdose or death. Abuse and misuse of benzodiazepines commonly involve concomitant use of other medications, alcohol, and/or illicit substances, which is associated with an increased frequency of serious adverse outcomes. Before prescribing diazepam rectal gel and throughout treatment, assess each patient’s risk for abuse, misuse, and addiction (see WARNINGS).
- The continued use of benzodiazepines may lead to clinically significant physical dependence. The risks of dependence and withdrawal increase with longer treatment duration and higher daily dose. Although diazepam rectal gel is indicated only for intermittent use (see INDICATIONS AND USAGEand DOSAGE AND ADMINISTRATION), if used more frequently than recommended, abrupt discontinuation or rapid dosage reduction of diazepam rectal gel may precipitate acute withdrawal reactions, which can be life-threatening. For patients using diazepam rectal gel more frequently than recommended, to reduce the risk of withdrawal reactions, use a gradual taper to discontinue diazepam rectal gel (see WARNINGS).

DESCRIPTION

Diazepam rectal gel rectal delivery system is a non-sterile diazepam gel provided in a prefilled, unit-dose, rectal delivery system. Diazepam rectal gel contains 5 mg/mL diazepam, benzoic acid, benzyl alcohol (1.5%), ethyl alcohol (10%), hydroxypropyl methylcellulose, propylene glycol, purified water, and sodium benzoate. Diazepam rectal gel is clear to slightly yellow and has a pH between 6.5-7.5.

Diazepam, the active ingredient of diazepam rectal gel, is a benzodiazepine anticonvulsant with the chemical name 7-chloro-1,3-dihydro-1-methyl-5-phenyl-2 H-1,4-benzodiazepin-2-one. The structural formula is as follows:

CLINICAL PHARMACOLOGY

Mechanism of Action

Although the precise mechanism by which diazepam exerts its antiseizure effects is unknown, animal and in vitro studies suggest that diazepam acts to suppress seizures through an interaction with γ-aminobutyric acid (GABA) receptors of the A-type (GABAA). GABA, the major inhibitory neurotransmitter in the central nervous system (CNS), acts at this receptor to open the membrane channel allowing chloride ions to flow into neurons. Entry of chloride ions causes an inhibitory potential that reduces the ability of neurons to depolarize to the threshold potential necessary to produce action potentials. Excessive depolarization of neurons is implicated in the generation and spread of seizures. It is believed that diazepam enhances the actions of GABA by causing GABA to bind more tightly to the
GABAAreceptor.

Pharmacokinetics

Pharmacokinetic information of diazepam following rectal administration was obtained from studies conducted in healthy adult subjects. No pharmacokinetic studies were conducted in pediatric patients. Therefore, information from the literature is used to define pharmacokinetic labeling in the pediatric population.

Diazepam rectal gel is well absorbed following rectal administration, reaching peak plasma concentrations in 1.5 hours. The absolute bioavailability of diazepam rectal gel relative to Valium injectable is 90%. The volume of distribution of diazepam rectal gel is calculated to be approximately 1 L/kg. The mean elimination half-life of diazepam and desmethyldiazepam following administration of a 15 mg dose of diazepam rectal gel was found to be about 46 hours (CV=43%) and 71 hours (CV=37%), respectively.
Both diazepam and its major active metabolite desmethyldiazepam bind extensively to plasma proteins (95-98%).

FIGURE 1:Plasma Concentrations of Diazepam and Desmethyldiazepam Following Diazepam Rectal Gel or IV Diazepam

Metabolism and Elimination:It has been reported in the literature that diazepam is extensively metabolized to one major active metabolite (desmethyldiazepam) and two minor active metabolites, 3-hydroxydiazepam (temazepam) and 3-hydroxy-N-diazepam (oxazepam) in plasma. At therapeutic doses, desmethyldiazepam is found in plasma at concentrations equivalent to those of diazepam while oxazepam and temazepam are not usually detectable. The metabolism of diazepam is primarily hepatic and involves demethylation (involving primarily CYP2C19 and CYP3A4) and 3-hydroxylation (involving primarily CYP3A4), followed by glucuronidation. The marked inter-individual variability in the clearance of diazepam reported in the literature is probably attributable to variability of CYP2C19 (which is known to exhibit genetic polymorphism; about 3-5% of Caucasians have little or no activity and are “poor metabolizers”) and CYP3A4. No inhibition was demonstrated in the presence of inhibitors selective for CYP2A6, CYP2C9, CYP2D6, CYP2E1, or CYP1A2, indicating that these enzymes are not significantly involved in metabolism of diazepam.

Special Populations

Hepatic Impairment:

No pharmacokinetic studies were conducted with diazepam rectal gel in hepatically impaired subjects. Literature review indicates that following administration of 0.1 to 0.15 mg/kg of diazepam intravenously, the half-life of diazepam was prolonged by two to five-fold in subjects with alcoholic cirrhosis (n=24) compared to age-matched control subjects (n=37) with a corresponding decrease in clearance by half: however, the exact degree of hepatic impairment in these subjects was not characterized in this literature (see PRECAUTIONS).

Renal Impairment:

The pharmacokinetics of diazepam have not been studied in renally impaired subjects (see PRECAUTIONS).

Pediatrics:

No pharmacokinetic studies were conducted with diazepam rectal gel in the pediatric population. However, literature review indicates that following IV administration (0.33 mg/kg), diazepam has a longer half-life in neonates (birth up to one month; approximately 50-95 hours) and infants (one month up to two years; about 40-50 hours), whereas it has a shorter half-life in children (two to 12 years; approximately 15-21 hours) and adolescents (12 to 16 years; about 18-20 hours) (see PRECAUTIONS).

Elderly:

A study of single dose IV administration of diazepam (0.1 mg/kg) indicates that the elimination half-life of diazepam increases linearly with age, ranging from about 15 hours at 18 years (healthy young adults) to about 100 hours at 95 years (healthy elderly) with a corresponding decrease in clearance of free diazepam (see PRECAUTIONSand DOSAGE AND ADMINISTRATION).

Effect of Gender, Race, and Cigarette Smoking:

No targeted pharmacokinetic studies have been conducted to evaluate the effect of gender, race, and cigarette smoking on the pharmacokinetics of diazepam. However, covariate analysis of a population of treated patients following administration of diazepam rectal gel, indicated that neither gender nor cigarette smoking had any effect on the pharmacokinetics of diazepam.

Clinical Studies

The effectiveness of diazepam rectal gel has been established in two adequate and well controlled clinical studies in children and adults exhibiting the seizure pattern described below under INDICATIONS AND USAGE.

A randomized, double-blind study compared sequential doses of diazepam rectal gel and placebo in 91 patients (47 children, 44 adults) exhibiting the appropriate seizure profile. The first dose was given at the onset of an identified episode. Children were dosed again four hours after the first dose and were observed for a total of 12 hours. Adults were dosed at four and 12 hours after the first dose and were observed for a total of 24 hours. Primary outcomes for this study were seizure frequency during the period of observation and a global assessment that took into account the severity and nature of the seizures as well as their frequency.

The median seizure frequency for the diazepam rectal gel treated group was zero seizures per hour, compared to a median seizure frequency of 0.3 seizures per hour for the placebo group, a difference that was statistically significant (p <0.0001). All three categories of the global assessment (seizure frequency, seizure severity, and “overall”) were also found to be statistically significant in favor of diazepam rectal gel (p < 0.0001). The following histogram displays the results for the “overall” category of the global assessment.

FIGURE 2: Caregiver Overall Global Assessment of the Efficacy of Diazepam Rectal Gel

Patients treated with diazepam rectal gel experienced prolonged time-to-next-seizure compared to placebo (p = 0.0002) as shown in the following graph.

FIGURE 3: Kaplan-Meier Survival Analysis of Time-to-Next-Seizure — First Study

In addition, 62% of patients treated with diazepam rectal gel were seizure-free during the observation period compared to 20% of placebo patients.

Analysis of response by gender and age revealed no substantial differences between treatment in either of these subgroups. Analysis of response by race was considered unreliable, due to the small percentage of non-Caucasians.

A second double-blind study compared single doses of diazepam rectal gel and placebo in 114 patients (53 children, 61 adults). The dose was given at the onset of the identified episode and patients were observed for a total of 12 hours. The primary outcome in this study was seizure frequency. The median seizure frequency for the diazepam rectal gel-treated group was zero seizures per 12 hours, compared to a median seizure frequency of 2.0 seizures per 12 hours for the placebo group, a difference that was statistically significant (p < 0.03). Patients treated with diazepam rectal gel experienced prolonged time-to-next-seizure compared to placebo (p = 0.0072) as shown in the following graph.

In addition, 55% of patients treated with diazepam rectal gel were seizure-free during the observation period compared to 34% of patients receiving placebo. Overall, caregivers judged diazepam rectal gel to be more effective than placebo (p = 0.018), based on a 10 centimeter visual analog scale. In addition, investigators also evaluated the effectiveness of diazepam rectal gel and judged diazepam rectal gel to be more effective than placebo (p < 0.001).

An analysis of response by gender revealed a statistically significant difference between treatments in females but not in males in this study, and the difference between the 2 genders in response to the treatments reached borderline statistical significance. Analysis of response by race was considered unreliable, due to the small percentage of non-Caucasians.

INDICATIONS AND USAGE

Diazepam rectal gel is intended for the acute treatment of intermittent, stereotypic episodes of frequent seizure activity (i.e., seizure clusters, acute repetitive seizures) that are distinct from a patient’s usual seizure pattern in patients with epilepsy 2 years of age and older.

CONTRAINDICATIONS

Diazepam rectal gel is contraindicated in patients with a known hypersensitivity to diazepam. Diazepam rectal gel may be used in patients with open angle glaucoma who are receiving appropriate therapy but is contraindicated in acute narrow angle glaucoma.

WARNINGS

General

Diazepam rectal gel should only be administered by caregivers who in the opinion of the prescribing physician 1) are able to distinguish the distinct cluster of seizures (and/or the events presumed to herald their onset) from the patient’s ordinary seizure activity, 2) have been instructed and judged to be competent to administer the treatment rectally, 3) understand explicitly which seizure manifestations may or may not be treated with diazepam rectal gel, and 4) are able to monitor the clinical response and recognize when that response is such that immediate professional medical evaluation is required.

Risks from Concomitant Use with Opioids

Concomitant use of benzodiazepines, including diazepam rectal gel and diazepam rectal gel rectal delivery system, and opioids may result in profound sedation, respiratory depression, coma, and death. Because of these risks, reserve concomitant prescribing of benzodiazepines and opioids for patients for whom alternative treatment options are inadequate.

Observational studies have demonstrated that concomitant use of opioid analgesics and benzodiazepines increases the risk of drug-related mortality compared to use of opioids alone. If a decision is made to
prescribe diazepam rectal gel or diazepam rectal gel rectal delivery system concomitantly with opioids, prescribe the lowest effective dosages and minimum durations of concomitant use, and follow patients closely for signs and symptoms of respiratory depression and sedation. Advise both patients and caregivers about the risks of respiratory depression and sedation when diazepam rectal gel or diazepam rectal gel rectal delivery system is used with opioids (see PRECAUTIONS).

Abuse, Misuse, and Addiction

The use of benzodiazepines, including diazepam rectal gel, exposes users to the risks of abuse, misuse, and addiction, which can lead to overdose or death. Abuse and misuse of benzodiazepines often (but not always) involve the use of doses greater than the maximum recommended dosage and commonly involve concomitant use of other medications, alcohol, and/or illicit substances, which is associated with an increased frequency of serious adverse outcomes, including respiratory depression, overdose, or death (see DRUG ABUSE AND DEPENDENCE: Abuse).

Before prescribing diazepam rectal gel and throughout treatment, assess each patient’s risk for abuse, misuse, and addiction. Use of diazepam rectal gel, particularly in patients at elevated risk, necessitates counseling about the risks and proper use of diazepam rectal gel along with monitoring for signs and symptoms of abuse, misuse, and addiction. Do not exceed the recommended dosing frequency; avoid or minimize concomitant use of CNS depressants and other substances associated with abuse, misuse, and addiction (e.g., opioid analgesics, stimulants); and advise patients on the proper disposal of unused drug. If a substance use disorder is suspected, evaluate the patient and institute (or refer them for) early treatment, as appropriate.

Dependence and Withdrawal Reactions After Use of Diazepam Rectal Gel More Frequently Than Recommended

For patients using diazepam rectal gel more frequently than recommended, to reduce the risk of withdrawal reactions, use a gradual taper to discontinue diazepam rectal gel (a patient-specific plan should be used to taper the dose).

Patients at an increased risk of withdrawal adverse reactions after benzodiazepine discontinuation or rapid dosage reduction include those who take higher dosages, and those who have had longer durations of use.

Acute Withdrawal Reactions
The continued use of benzodiazepines may lead to clinically significant physical dependence. Although diazepam rectal gel is indicated only for intermittent use (see INDICATIONS AND USAGEand DOSAGE AND ADMINISTRATION), if used more frequently than recommended, abrupt discontinuation or rapid dosage reduction of diazepam rectal gel, or administration of flumazenil (a benzodiazepine antagonist) may precipitate acute withdrawal reactions, which can be life-threatening (e.g., seizures) (see DRUG ABUSE AND DEPENDENCE: Dependence) .

Protracted Withdrawal Syndrome

In some cases, benzodiazepine users have developed a protracted withdrawal syndrome with withdrawal symptoms lasting weeks to more than 12 months (see DRUG ABUSE AND DEPENDENCE: Dependence).

CNS Depression

Because diazepam rectal gel produces CNS depression, patients receiving this drug who are otherwise capable and qualified to do so should be cautioned against engaging in hazardous occupations requiring mental alertness, such as operating machinery, driving a motor vehicle, or riding a bicycle until they have completely returned to their level of baseline functioning.

Although diazepam rectal gel is indicated for use solely on an intermittent basis, the potential for a synergistic CNS-depressant effect when used simultaneously with alcohol or other CNS depressants must be considered by the prescribing physician, and appropriate recommendations made to the patient and/or caregiver.

Prolonged CNS depression has been observed in neonates treated with diazepam. Therefore, diazepam rectal gel is not recommended for use in children under six months of age.

Neonatal Sedation and Withdrawal Syndrome
Use of diazepam rectal gel late in pregnancy can result in sedation (respiratory depression, lethargy, hypotonia) and/or withdrawal symptoms (hyperreflexia, irritability, restlessness, tremors, inconsolable crying, and feeding difficulties) in the neonate (see PRECAUTIONS: Pregnancy). Monitor neonates exposed to diazepam rectal gel during pregnancy or labor for signs of sedation and monitor neonates exposed to diazepam rectal gel during pregnancy for signs of withdrawal; manage these neonates accordingly.

Chronic Use
Diazepam rectal gel is not recommended for chronic, daily use as an anticonvulsant because of the potential for development of tolerance to diazepam. Chronic daily use of diazepam may increase the frequency and/or severity of tonic clonic seizures, requiring an increase in the dosage of standard anticonvulsant medication. In such cases, abrupt withdrawal of chronic diazepam may also be associated with a temporary increase in the frequency and/or severity of seizures.

Use in Patients with Petit Mal Status
Tonic status epilepticushas been precipitated in patients treated with IV diazepam for petit mal status or petit mal variant status.

PRECAUTIONS

Information for Patients
Risks from Concomitant Use with Opioids:Inform patients and caregivers that potentially fatal additive
effects may occur if diazepam rectal gel or diazepam rectal gel rectal delivery system is used with opioids and not to use such drugs concomitantly unless supervised by a health care provider (see WARNINGSand PRECAUTIONS: Drug Interactions).

Abuse, Misuse, and Addiction:Inform patients that the use of diazepam rectal gel more frequently than recommended, even at recommended dosages, exposes users to risks of abuse, misuse, and addiction, which can lead to overdose and death, especially when used in combination with other medications (e.g., opioid analgesics), alcohol, and/or illicit substances. Inform patients about the signs and symptoms of benzodiazepine abuse, misuse, and addiction; to seek medical help if they develop these signs and/or symptoms; and on the proper disposal of unused drug (see WARNINGS: Abuse, Misuse, and Addictionand DRUG ABUSE AND DEPENDENCE).

Withdrawal Reactions:Inform patients that use of diazepam rectal gel more frequently than recommended may lead to clinically significant physical dependence and that abrupt discontinuation or rapid dosage reduction of diazepam rectal gel may precipitate acute withdrawal reactions, which can be life-threatening. Inform patients that in some cases, patients taking benzodiazepines have developed a protracted withdrawal syndrome with withdrawal symptoms lasting weeks to more than 12 months (see WARNINGS: Dependence and Withdrawal Reactionsand DRUG ABUSE AND DEPENDENCE).

Administration:Prescribers are strongly advised to take all reasonable steps to ensure that caregivers fully understand their role and obligations vis a vis the administration of diazepam rectal gel to individuals in their care. Prescribers should routinely discuss the steps in the Patient/Caregiver Package Insert (see Patient/Caregiver Insert printed at the end of the product labeling and also included in the product carton). The successful and safe use of diazepam rectal gel depends in large measure on the competence and performance of the caregiver.

Prescribers should advise caregivers that they expect to be informed immediately if a patient develops any new findings which are not typical of the patient’s characteristic seizure episode.

Interference With Cognitive and Motor Performance:Because benzodiazepines have the potential to impair judgment, thinking, or motor skills, patients should be cautioned about operating hazardous machinery, including automobiles, until they are reasonably certain that diazepam rectal gel therapy does not affect them adversely.

Pregnancy

Advise pregnant females that use of diazepam rectal gel late in pregnancy can result in sedation (respiratory depression, lethargy, hypotonia) and/or withdrawal symptoms (hyperreflexia, irritability, restlessness, tremors, inconsolable crying, and feeding difficulties) in newborns (see WARNINGS: Neonatal Sedation and Withdrawal Syndromeand PRECAUTIONS: Pregnancy). Instruct patients to inform their healthcare provider if they are pregnant.

Encourage patients to enroll in the North American Antiepileptic Drug (NAAED) Pregnancy Registry if they become pregnant while taking diazepam rectal gel. The registry is collecting information about the safety of antiepileptic drugs during pregnancy (see PRECAUTIONS: Pregnancy).

Lactation
Counsel patients that diazepam, the active ingredient in diazepam rectal gel, is present in breast milk. Instruct patients to inform their healthcare provider if they are breastfeeding or plan to breastfeed. Instruct breastfeeding patients who take diazepam rectal gel to monitor their infants for excessive sedation, poor feeding and poor weight gain, and to seek medical attention if they notice these signs (see PRECAUTIONS: Nursing Mothers).

Concomitant Medication
Although diazepam rectal gel is indicated for use solely on an intermittent basis, the potential for a synergistic CNS-depressant effect when used simultaneously with alcohol or other CNS-depressants must be considered by the prescribing physician, and appropriate recommendations made to the patient and/or caregiver.
Drug Interactions
There have been no clinical studies or reports in literature to evaluate the interaction of rectally administered diazepam with other drugs. As with all drugs, the potential for interaction by a variety of mechanisms is a possibility.

Effect of Concomitant Use of Benzodiazepines and Opioids: The concomitant use of benzodiazepines and opioids increases the risk of respiratory depression because of actions at different receptor sites in the CNS that control respiration. Benzodiazepines interact at GABAAsites, and opioids interact primarily at mu receptors. When benzodiazepines and opioids are combined, the potential for benzodiazepines to significantly worsen opioid-related respiratory depression exists. Limit dosage and duration of concomitant use of benzodiazepines and opioids, and follow patients closely for respiratory depression and sedation.
Other Psychotropic Agents or Other CNS Depressants:If diazepam rectal gel is to be combined with other psychotropic agents or other CNS depressants, careful consideration should be given to the pharmacology of the agents to be employed particularly with known compounds which may potentiate the action of diazepam, such as phenothiazines, narcotics, barbiturates, MAO inhibitors and other antidepressants.
Cimetidine:The clearance of diazepam and certain other benzodiazepines can be delayed in association with cimetidine administration. The clinical significance of this is unclear.
Valproate: Valproate may potentiate the CNS-depressant effects of diazepam.
Effect of Other Drugs on Diazepam Metabolism: In vitro studies using human liver preparations suggest that CYP2C19 and CYP3A4 are the principal isozymes involved in the initial oxidative metabolism of diazepam. Therefore, potential interactions may occur when diazepam is given concurrently with agents that affect CYP2C19 and CYP3A4 activity. Potential inhibitors of CYP2C19 (e.g., cimetidine, quinidine, and tranylcypromine) and CYP3A4 (e.g., ketoconazole, troleandomycin, and clotrimazole) could decrease the rate of diazepam elimination, while inducers of CYP2C19 (e.g., rifampin) and CYP3A4 (e.g., carbamazepine, phenytoin, dexamethasone, and phenobarbital) could increase the rate of elimination of diazepam.
Effect of Diazepam on the Metabolism of Other Drugs: There are no reports as to which isozymes could be inhibited or induced by diazepam. But, based on the fact that diazepam is a substrate for CYP2C19 and CYP3A4, it is possible that diazepam may interfere with the metabolism of drugs which are substrates for CYP2C19, (e.g. omeprazole, propranolol, and imipramine) and CYP3A4 (e.g. cyclosporine, paclitaxel, terfenadine, theophylline, and warfarin) leading to a potential drug-drug interaction.
Carcinogenesis, Mutagenesis, Impairment of Fertility
The carcinogenic potential of rectal diazepam has not been evaluated. In studies in which mice and rats were administered diazepam in the diet at a dose of 75 mg/kg/day (approximately six and 12 times, respectively, the maximum recommended human dose [MRHD=1 mg/kg/day] on a mg/m^2basis) for 80 and 104 weeks, respectively, an increased incidence of liver tumors was observed in males of both species.
The data currently available are inadequate to determine the mutagenic potential of diazepam.
Reproduction studies in rats showed decreases in the number of pregnancies and in the number of surviving offspring following administration of an oral dose of 100 mg/kg/day (approximately 16 times the MRHD on a mg/m^2basis) prior to and during mating and throughout gestation and lactation. No adverse effects on fertility or offspring viability were noted at a dose of 80 mg/kg/day (approximately 13 times the MRHD on a mg/m^2basis).
Pregnancy
Pregnancy Exposure Registry
There is a pregnancy exposure registry that monitors pregnancy outcomes in women exposed to AEDs, such as diazepam rectal gel, during pregnancy. Healthcare providers are encouraged to recommend that pregnant women taking diazepam rectal gel enroll in the NAAED Pregnancy Registry by calling 1-888- 233-2334 or online at http://www.aedpregnancyregistry.org/.
Risk Summary
Neonates born to mothers using benzodiazepines late in pregnancy have been reported to experience symptoms of sedation and/or neonatal withdrawal (see WARNINGS: Neonatal Sedation and Withdrawal Syndrome and PRECAUTIONS: Pregnancy, Clinical Considerations). Available data from published observational studies of pregnant women exposed to benzodiazepines do not report a clear association with benzodiazepines and major birth defects (see Human Data).
In animal studies, administration of diazepam during the organogenesis period of pregnancy resulted in increased incidences of fetal malformations at doses greater than those used clinically. Data for diazepam and other benzodiazepines suggest the possibility of increased neuronal cell death and long-term effects on neurobehavioral and immunological function based on findings in animals following prenatal or early postnatal exposure at clinically relevant doses (see Animal Data).
The background risk of major birth defects and miscarriage for the indicated population is unknown. All pregnancies have a background risk of birth defect, loss, or other adverse outcomes. In the U.S. general population, the estimated risk of major birth defects and of miscarriage in clinically recognized pregnancies is 2% to 4% and 15% to 20%, respectively.
Clinical Considerations
Fetal/Neonatal Adverse Reactions
Benzodiazepines cross the placenta and may produce respiratory depression, hypotonia, and sedation in neonates. Monitor neonates exposed to diazepam rectal gel during pregnancy or labor for signs of sedation, respiratory depression, hypotonia, and feeding problems. Monitor neonates exposed to diazepam rectal gel during pregnancy for signs of withdrawal. Manage these neonates accordingly (see WARNINGS: Neonatal Sedation and Withdrawal Syndrome).
Data
Human Data
Published data from observational studies on the use of benzodiazepines during pregnancy do not report a clear association with benzodiazepines and major birth defects. Although early studies reported an increased risk of congenital malformations with diazepam and chlordiazepoxide, there was no consistent pattern noted. In addition, the majority of more recent case-control and cohort studies of benzodiazepine use during pregnancy, which were adjusted for confounding exposures to alcohol, tobacco and other medications, have not confirmed these findings.
Animal Data
Diazepam has been shown to produce increased incidences of fetal malformations in mice and hamsters when given orally at single doses of 100 mg/kg or greater (approximately 20 times the maximum recommended adult human dose [0.4 mg/kg/day] or greater on a mg/m^2basis). Cleft palate and exencephaly are the most common and consistently reported malformations produced in these species by administration of high, maternally-toxic doses of diazepam during organogenesis. In published animal studies, administration of benzodiazepines or other drugs that enhance GABAergic neurotransmission to neonatal rats has been reported to result in widespread apoptotic neurodegeneration in the developing brain at plasma concentrations relevant for seizure control in humans. The window of vulnerability to these changes in rats (postnatal days 0-14) includes a period of brain development that takes place during the third trimester of pregnancy in humans.
Nursing Mothers
Risk Summary
Diazepam is present in breastmilk. There are reports of sedation, poor feeding and poor weight gain in infants exposed to benzodiazepines through breast milk. There are no data on the effects of diazepam on milk production.
The developmental and health benefits of breastfeeding should be considered along with the mother’s clinical need for diazepam rectal gel and any potential adverse effects on the breastfed infant from diazepam rectal gel or from the underlying maternal condition.
Clinical Considerations
Infants exposed to diazepam rectal gel through breast milk should be monitored for sedation, poor feeding and poor weight gain. Because diazepam and its metabolites may be present in human breast milk for prolonged periods of time after acute use of diazepam rectal gel, patients should be advised not to breastfeed for an appropriate period of time after receiving treatment with diazepam rectal gel.
Caution in Renally Impaired Patients
Metabolites of diazepam rectal gel are excreted by the kidneys; to avoid their excess accumulation, caution should be exercised in the administration of the drug to patients with impaired renal function.
Caution in Hepatically Impaired Patients
Concomitant liver disease is known to decrease the clearance of diazepam (see CLINICAL PHARMACOLOGY: Special Populations, Hepatic Impairment). Therefore, diazepam rectal gel should be used with caution in patients with liver disease.
Use in Pediatrics
The controlled trials demonstrating the effectiveness of diazepam rectal gel included children two years of age and older. Clinical studies have not been conducted to establish the efficacy and safety of diazepam rectal gel in children under two years of age.
Use in Patients with Compromised Respiratory Function
Diazepam rectal gel should be used with caution in patients with compromised respiratory function related to a concurrent disease process (e.g., asthma, pneumonia) or neurologic damage.
Use in Elderly
In elderly patients diazepam rectal gel should be used with caution due to an increase in half-life with a corresponding decrease in the clearance of free diazepam. It is also recommended that the dosage be decreased to reduce the likelihood of ataxia or oversedation.

ADVERSE REACTIONS

Diazepam rectal gel adverse event data were collected from double-blind, placebo-controlled studies and open-label studies. The majority of adverse events were mild to moderate in severity and transient in nature.

Two patients who received diazepam rectal gel died seven to 15 weeks following treatment; neither of these deaths was deemed related to diazepam rectal gel.

The most frequent adverse event reported to be related to diazepam rectal gel in the two double-blind, placebo-controlled studies was somnolence (23%). Less frequent adverse events were dizziness, headache, pain, abdominal pain, nervousness, vasodilatation, diarrhea, ataxia, euphoria, incoordination, asthma, rhinitis, and rash, which occurred in approximately 2-5% of patients.

Approximately 1.4% of the 573 patients who received diazepam rectal gel in clinical trials of epilepsy discontinued treatment because of an adverse event. The adverse event most frequently associated with discontinuation (occurring in three patients) was somnolence. Other adverse events most commonly associated with discontinuation and occurring in two patients were hypoventilation and rash. Adverse events occurring in one patient were asthenia, hyperkinesia, incoordination, vasodilatation and urticaria. These events were judged to be related to diazepam rectal gel.

In the two domestic double-blind, placebo-controlled, parallel-group studies, the proportion of patients who discontinued treatment because of adverse events was 2% for the group treated with diazepam rectal gel, versus 2% for the placebo group. In the diazepam rectal gel group, the adverse events considered the primary reason for discontinuation were different in the two patients who discontinued treatment; one discontinued due to rash and one discontinued due to lethargy. The primary reason for discontinuation in the patients treated with placebo was lack of effect.

Adverse Event Incidence in Controlled Clinical Trials

Table 1 lists treatment-emergent signs and symptoms that occurred in > 1% of patients enrolled in parallel-group, placebo-controlled trials and were numerically more common in the diazepam rectal gel group. Adverse events were usually mild or moderate in intensity.

The prescriber should be aware that these figures, obtained when diazepam rectal gel was added to concurrent antiepileptic drug therapy, cannot be used to predict the frequency of adverse events in the course of usual medical practice when patient characteristics and other factors may differ from those prevailing during clinical studies. Similarly, the cited frequencies cannot be directly compared with figures obtained from other clinical investigations involving different treatments, uses, or investigators. An inspection of these frequencies, however, does provide the prescribing physician with one basis to estimate the relative contribution of drug and non-drug factors to the adverse event incidences in the population studied.

Table 1: Treatment-Emergent Signs and Symptoms That Occurred in > 1% Of Patients Enrolled in Parallel-Group, Placebo-Controlled Trials and Were Numerically More Common in the Diazepam Rectal Gel Group
 |  | Diazepam Rectal Gel | Placebo
Body System | COSTART Term | N = 101 % | N = 104 %
Body As A Whole | Headache | 5% | 4%
Cardiovascular | Vasodilatation | 2% | 0%
Digestive | Diarrhea | 4% | <1%
Nervous | Ataxia | 3% | <1%
 | Dizziness | 3% | 2%
 | Euphoria | 3% | 0%
 | Incoordination | 3% | 0%
 | Somnolence | 23% | 8%
Respiratory | Asthma | 2% | 0%
Skin and Appendages | Rash | 3% | 0%

Other events reported by 1% or more of patients treated in controlled trials but equally or more frequent in the placebo group than in the diazepam rectal gel group were abdominal pain, pain, nervousness, and rhinitis. Other events reported by fewer than 1% of patients were infection, anorexia, vomiting, anemia, lymphadenopathy, grand mal convulsion, hyperkinesia, cough increased, pruritus, sweating, mydriasis, and urinary tract infection.

The pattern of adverse events was similar for different age, race and gender groups.

Other Adverse Events Observed During All Clinical Trials

Diazepam rectal gel has been administered to 573 patients with epilepsy during all clinical trials, only some of which were placebo-controlled. During these trials, all adverse events were recorded by the clinical investigators using terminology of their own choosing. To provide a meaningful estimate of the proportion of individuals having adverse events, similar types of events were grouped into a smaller number of standardized categories using modified COSTART dictionary terminology. These categories are used in the listing below. All of the events listed below occurred in at least 1% of the 573 individuals exposed to diazepam rectal gel.

All reported events are included except those already listed above, events unlikely to be drug-related, and those too general to be informative. Events are included without regard to determination of a causal relationship to diazepam.

BODY AS A WHOLE: Asthenia

CARDIOVASCULAR:Hypotension, vasodilatation

NERVOUS:Agitation, confusion, convulsion, dysarthria, emotional lability, speech disorder, thinking abnormal, vertigo

RESPIRATORY: Hiccup

The following infrequent adverse events were not seen with diazepam rectal gel but have been reported previously with diazepam use: depression, slurred speech, syncope, constipation, changes in libido, urinary retention, bradycardia, cardiovascular collapse, nystagmus, urticaria, neutropenia and jaundice.

Paradoxical reactions such as acute hyperexcited states, anxiety, hallucinations, increased muscle spasticity, insomnia, rage, sleep disturbances and stimulation have been reported with diazepam; should these occur, use of diazepam rectal gel should be discontinued.

To report SUSPECTED ADVERSE REACTIONS, contact Oceanside Pharmaceuticals at 1-800-321-4576 or FDA at 1-800-FDA-1088 or www.fda.gov/medwatch.

DRUG ABUSE AND DEPENDENCE

Controlled Substance:Diazepam rectal gel contains diazepam, a Schedule IV controlled substance.

Abuse: Diazepam rectal gel is a benzodiazepine and a CNS depressant with a potential for abuse and addiction. Abuse is the intentional, non-therapeutic use of a drug, even once, for its desirable psychological or physiological effects. Misuse is the intentional use, for therapeutic purposes, of a drug by an individual in a way other than prescribed by a health care provider or for whom it was not prescribed. Drug addiction is a cluster of behavioral, cognitive, and physiological phenomena that may include a strong desire to take the drug, difficulties in controlling drug use (e.g., continuing drug use despite harmful consequences, giving a higher priority to drug use than other activities and obligations), and possible tolerance or physical dependence. Even taking benzodiazepines as prescribed may put patients at risk for abuse and misuse of their medication. Abuse and misuse of benzodiazepines may lead to addiction.

Abuse and misuse of benzodiazepines often (but not always) involve the use of doses greater than the maximum recommended dosage and commonly involve concomitant use of other medications, alcohol, and/or illicit substances, which is associated with an increased frequency of serious adverse outcomes, including respiratory depression, overdose, or death. Benzodiazepines are often sought by individuals who abuse drugs and other substances, and by individuals with addictive disorders (see WARNINGS, Abuse, Misuse, and Addiction).

The following adverse reactions have occurred with benzodiazepine abuse and/or misuse: abdominal pain, amnesia, anorexia, anxiety, aggression, ataxia, blurred vision, confusion, depression, disinhibition, disorientation, dizziness, euphoria, impaired concentration and memory, indigestion, irritability, muscle pain, slurred speech, tremors, and vertigo.

The following severe adverse reactions have occurred with benzodiazepine abuse and/or misuse: delirium, paranoia, suicidal ideation and behavior, seizures, coma, breathing difficulty, and death. Death is more often associated with polysubstance use (especially benzodiazepines with other CNS depressants such as opioids and alcohol).

Dependence:

Physical Dependence After Use of Diazepam Rectal Gel More Frequently Than Recommended

Diazepam rectal gel may produce physical dependence if used more frequently than recommended. Physical dependence is a state that develops as a result of physiological adaptation in response to repeated drug use, manifested by withdrawal signs and symptoms after abrupt discontinuation or a significant dose reduction of a drug. Although diazepam rectal gel is indicated only for intermittent use (see INDICATIONS AND USAGEand DOSAGE AND ADMINISTRATION) ,if used more frequently than recommended, abrupt discontinuation or rapid dosage reduction or administration of flumazenil, a benzodiazepine antagonist, may precipitate acute withdrawal reactions, including seizures, which can be life-threatening. Patients at an increased risk of withdrawal adverse reactions after benzodiazepine discontinuation or rapid dosage reduction include those who take higher dosages (i.e., higher and/or more frequent doses) and those who have had longer durations of use (see WARNINGS, Dependence and Withdrawal Reactions).

For patients using diazepam rectal gel more frequently than recommended, to reduce the risk of withdrawal reactions, use a gradual taper to discontinue diazepam rectal gel (see WARNINGS, Dependence and Withdrawal Reactions).

Acute Withdrawal Signs and Symptoms

Acute withdrawal signs and symptoms associated with benzodiazepines have included abnormal involuntary movements, anxiety, blurred vision, depersonalization, depression, derealization, dizziness, fatigue, gastrointestinal adverse reactions (e.g., nausea, vomiting, diarrhea, weight loss, decreased appetite), headache, hyperacusis, hypertension, irritability, insomnia, memory impairment, muscle pain and stiffness, panic attacks, photophobia, restlessness, tachycardia, and tremor. More severe acute withdrawal signs and symptoms, including life-threatening reactions, have included catatonia, convulsions, delirium tremens, depression, hallucinations, mania, psychosis, seizures, and suicidality.

Protracted Withdrawal Syndrome

Protracted withdrawal syndrome associated with benzodiazepines is characterized by anxiety, cognitive impairment, depression, insomnia, formication, motor symptoms (e.g., weakness, tremor, muscle twitches), paresthesia, and tinnitus that persists beyond 4 to 6 weeks after initial benzodiazepine withdrawal. Protracted withdrawal symptoms may last weeks to more than 12 months. As a result, there may be difficulty in differentiating withdrawal symptoms from potential re-emergence or continuation of symptoms for which the benzodiazepine was being used.

Tolerance

Tolerance to diazepam rectal gel may develop after use more frequently than recommended. Tolerance is a physiological state characterized by a reduced response to a drug after repeated administration (i.e., a higher dose of a drug is required to produce the same effect that was once obtained at a lower dose). Tolerance to the therapeutic effect of benzodiazepines may develop; however, little tolerance develops to the amnestic reactions and other cognitive impairments caused by benzodiazepines.

OVERDOSAGE

Overdosage of benzodiazepines is characterized by central nervous system depression ranging from drowsiness to coma. In mild to moderate cases, symptoms can include drowsiness, confusion, dysarthria, lethargy, hypnotic state, diminished reflexes, ataxia, and hypotonia. Rarely, paradoxical or disinhibitory reactions (including agitation, irritability, impulsivity, violent behavior, confusion, restlessness, excitement, and talkativeness) may occur. In severe overdosage cases, patients may develop respiratory depression and coma. Overdosage of benzodiazepines in combination with other CNS depressants (including alcohol and opioids) may be fatal (see WARNINGS: Abuse, Misuse, and Addiction). Markedly abnormal (lowered or elevated) blood pressure, heart rate, or respiratory rate raise the concern that additional drugs and/or alcohol are involved in the overdosage.

In managing benzodiazepine overdosage, employ general supportive measures, including intravenous fluids and airway maintenance. Flumazenil, a specific benzodiazepine receptor antagonist indicated for the complete or partial reversal of the sedative effects of benzodiazepines in the management of benzodiazepine overdosage, can lead to withdrawal and adverse reactions, including seizures, particularly in the context of mixed overdosage with drugs that increase seizure risk (e.g., tricyclic and tetracyclic antidepressants) and in patients with long-term benzodiazepine use and physical dependency. The risk of withdrawal seizures with flumazenil use may be increased in patients with epilepsy. Flumazenil is contraindicated in patients who have received a benzodiazepine for control of a potentially life-threatening condition (e.g., status epilepticus). If the decision is made to use flumazenil, it should be used as an adjunct to, not as a substitute for, supportive management of benzodiazepine overdosage. See the flumazenil injection Prescribing Information.

Consider contacting the Poison Help line (1-800-221-2222) or a medical toxicologist for additional overdosage management recommendations.

DOSAGE AND ADMINISTRATION

(see also Patient/Caregiver Package Insert)

This section is intended primarily for the prescriber; however, the prescriber should also be aware of the dosing information and directions for use provided in the patient package insert.

A decision to prescribe diazepam rectal gel involves more than the diagnosis and the selection of the correct dose for the patient.

First, the prescriber must be convinced from historical reports and/or personal observations that the patient exhibits the characteristic identifiable seizure cluster that can be distinguished from the patient’s usual seizure activity by the caregiver who will be responsible for administering diazepam rectal gel.

Second, because diazepam rectal gel is only intended for adjunctive use, the prescriber must ensure that the patient is receiving an optimal regimen of standard anti-epileptic drug treatment and is, nevertheless, continuing to experience these characteristic episodes.

Third, because a non-health professional will be obliged to identify episodes suitable for treatment, make the decision to administer treatment upon that identification, administer the drug, monitor the patient, and assess the adequacy of the response to treatment, a major component of the prescribing process involves the necessary instruction of this individual.

Fourth, the prescriber and caregiver must have a common understanding of what is and is not an episode of seizures that is appropriate for treatment, the timing of administration in relation to the onset of the episode, the mechanics of administering the drug, how and what to observe following administration, and what would constitute an outcome requiring immediate and direct medical attention.

Calculating Prescribed Dose

The diazepam rectal gel dose should be individualized for maximum beneficial effect. The recommended dose of diazepam rectal gel is 0.2-0.5 mg/kg depending on age. See the dosing table for specific recommendations.

Age (years) | Recommended Dose
2 through 5 | 0.5 mg/kg
6 through 11 | 0.3 mg/kg
12 and older | 0.2 mg/kg

Because diazepam rectal gel is provided as unit doses of 2.5, 5, 7.5, 10, 12.5, 15, 17.5, and 20 mg, the prescribed dose is obtained by rounding upward to the next available dose. The following table provides acceptable weight ranges for each dose and age category, such that patients will receive between 90% and 180% of the calculated recommended dose. The safety of this strategy has been established in clinical trials.

2 - 5 Years |  | 6 - 11 Years |  | 12+ Years
0.5 mg/kg |  | 0.3 mg/kg |  | 0.2 mg/kg
Weight | Dose | Weight | Dose | Weight | Dose
(kg) | (mg) | (kg) | (mg) | (kg) | (mg)
6 to 10 | 5 | 10 to 16 | 5 | 14 to 25 | 5
11 to 15 | 7.5 | 17 to 25 | 7.5 | 26 to 37 | 7.5
16 to 20 | 10 | 26 to 33 | 10 | 38 to 50 | 10
21 to 25 | 12.5 | 34 to 41 | 12.5 | 51 to 62 | 12.5
26 to 30 | 15 | 42 to 50 | 15 | 63 to 75 | 15
31 to 35 | 17.5 | 51 to 58 | 17.5 | 76 to 87 | 17.5
36 to 44 | 20 | 59 to 74 | 20 | 88 to 111 | 20

The rectal delivery system includes a plastic applicator with a flexible, molded tip available in two lengths. The diazepam rectal gel rectal delivery system 10 mg syringe is available with a 4.4 cm tip and the diazepam rectal gel rectal delivery system 20 mg syringe is available with a 6.0 cm tip. Diazepam rectal gel 2.5 mg is also available with a 4.4 cm tip.

In elderly and debilitated patients, it is recommended that the dosage be adjusted downward to reduce the likelihood of ataxia or oversedation.

The prescribed dose of diazepam rectal gel should be adjusted by the physician periodically to reflect changes in the patient’s age or weight.

The diazepam rectal gel 2.5 mg dose may also be used as a partial replacement dose for patients who may expel a portion of the first dose.

Additional Dose

The prescriber may wish to prescribe a second dose of diazepam rectal gel. A second dose, when required, may be given 4-12 hours after the first dose.

Treatment Frequency

It is recommended that diazepam rectal gel be used to treat no more than five episodes per month and no more than one episode every five days.

HOW SUPPLIED

Diazepam rectal gel rectal delivery system is a non-sterile, prefilled, unit dose, rectal delivery system. The rectal delivery system includes a plastic applicator with a flexible, molded tip available in two lengths, designated for convenience as 10 mg Delivery System and 20 mg Delivery System. The available doses from 20 mg delivery system are 12.5 mg, 15 mg, 17.5 mg and 20 mg. The available doses from 10 mg delivery system are 5 mg, 7.5 mg and 10 mg. The diazepam rectal gel delivery system is available in the following three presentations:

Diazepam Rectal Gel | Rectal Tip Size | NDC
2.5 mg Twin Pack | 4.4 cm | 68682-650-20
Diazepam Rectal Gel Rectal Delivery System | Rectal Tip Size | NDC
10 mg Delivery | 4.4 cm | 68682-652-20
System Twin Pack
20 mg Delivery | 6.0 cm | 68682-655-20
System Twin Pack

Each Twin Pack contains two diazepam rectal gel delivery systems, two packets of lubricating jelly, and administration and disposal Instructions available on the bottom of the package. Diazepam rectal gel rectal delivery system is also packed with Instructions for Caregivers upon receipt from pharmacy.

Store at 25°C (77°F); excursions permitted to 15°C to 30°C (59°F to 86°F) [see USP Controlled Room Temperature].

Diazepam Rectal Gel Rectal Delivery System

INSTRUCTIONS FOR CAREGIVERSUPON RECEIPTFROM PHARMACY

- Remove the syringe from the case.
- Confirm the dose prescribed by your doctor is visible and if known, is correct.

FOR EACH SYRINGE:

- Confirm that the prescribed dose is visible in the dose display window.
- Confirm that the green “READY” band is visible.
- Return the syringe to the case.

SEE PHARMACIST IF YOU HAVE ANY QUESTIONS ABOUT THESE INSTRUCTIONS.

The Instructions are also available on the bottom of each drug product package.

CAUTION: Federal law prohibits the transfer of this drug to any person other than the patient for whom it was prescribed.

Distributed by:
Oceanside Pharmaceuticals, a division of
Bausch Health US, LLC
Bridgewater, NJ 08807 USA

Manufactured by:
DPT Laboratories, Ltd.
San Antonio, TX 78215 USA

© 2023 Bausch Health Companies Inc. or its affiliates

9570805
Rev. 07/2023

ADMINISTRATION
AND DISPOSAL INSTRUCTIONS
Diazepam Rectal Gel and
Diazepam Rectal Gel Delivery System C-IV

IMPORTANT

Read first before using

To the caregiver using Diazepam Rectal Gel:
Please do not give Diazepam Rectal Gel until:

1. You have thoroughly read these instructions
2. Reviewed administration steps with the doctor
3. Understand the directions

To the caregiver using Diazepam Rectal Gel 10 mg rectal delivery system or 20 mg rectal delivery system:

Please do not give Diazepam Rectal Gel 10 mg rectal delivery system or 20 mg rectal delivery system until:

1. You have confirmed:
2. Prescribed dose is visible and if known,
  is correct
3. green “READY” band is visible
4. You have thoroughly read these instructions
5. Reviewed administration steps with the doctor
6. Understand the directions

Please do not administer Diazepam Rectal Gel until you feel comfortable with how to use Diazepam Rectal Gel. The doctor will tell you exactly when to use Diazepam Rectal Gel. When you use Diazepam Rectal Gel correctly and safely you will help bring seizures under control. Be sure to discuss every aspect of your role with the doctor. If you are not comfortable, then discuss your role with the doctor again.

To help the person with seizures:

- You must be able to tell the difference between cluster and ordinary seizures.
- You must be comfortable and satisfied that you are able to give Diazepam Rectal Gel.
- You need to agree with the doctor on the exact conditions when to treat with Diazepam Rectal Gel.
- You must know how and for how long you should check the person after giving Diazepam Rectal Gel.

To know what responses to expect:

- You need to know how soon seizures should stop or decrease in frequency after giving Diazepam Rectal Gel.
- You need to know what you should do if the seizures do not stop or there is a change in the person’s breathing, behavior or condition that alarms you.

If you have any questions or feel unsure about using the treatment, CALL THE DOCTORbefore using Diazepam Rectal Gel.

When to treat. Based on the doctor’s directions or prescription. Your doctor may prescribe a second dose of diazepam rectal gel. If a second dose is needed, give it 4 hours to 12 hours after the first dose.

________________________________________________________

________________________________________________________

Special considerations.

Diazepam Rectal Gel should be used with caution:

- In people with respiratory (breathing) difficulties (e.g., asthma or pneumonia)
- In the elderly
- In women of child bearing potential, pregnancy and nursing mothers

Discuss beforehand with the doctor any additional steps you may need to take if there is leakage of Diazepam Rectal Gel or a bowel movement.

Patient’s Diazepam Rectal Gel dosage is:__________mg

Patient’s resting breathing rate _________ Patient’s current weight ____________

Confirm current weight is still the same as when Diazepam Rectal Gel was prescribed ____________

Check expiration date and always remove cap before using. Be sure seal pin is removed with the cap.

TREATMENT 1
------------------------------------------------------------------------------------------------------------

Important things to tell the doctor:

Things to do after treatment with Diazepam Rectal Gel:

Stay with the person for 4 hours and make notes on the following:

- Changes in resting breathing rate________________________________________________
- Changes in color ____________________________________________________________
- Possible side effects from treatment _____________________________________________
- Your doctor may prescribe a second dose of diazepam rectal gel. If a second dose is needed, give it 4 hours to 12 hours after the first dose.

TREATMENT 2
------------------------------------------------------------------------------------------------------------

Important things to tell the doctor:

Things to do after treatment with Diazepam Rectal Gel:

Stay with the person for 4 hours and make notes on the following:

- Changes in resting breathing rate__________________________________________________
- Changes in color ____________________________________________________________
- Possible side effects from treatment_________________________________________________

ADMINISTRATION
AND DISPOSAL
INSTRUCTIONS

CIV
Diazepam Rectal Gel and
Diazepam Rectal Gel Delivery System

Distributed by:
Oceanside Pharmaceuticals, a division of
Bausch Health US, LLC
Bridgewater, NJ 08807 USA
Manufactured by:
DPT Laboratories, Ltd.
San Antonio, TX 78215 USA

© 2023 Bausch Health Companies Inc. or its affiliates

Revised: 07/2023
9570805

PRINCIPAL DISPLAY PANEL - 10 mg Rectal Gel Label

NDC68682-652-20

Rx only

DIAZEPAM RECTAL GEL CIV

10 mgDelivery System

For Rectal Administration Only

LOT:

EXP:

Refer to package
insert for prescribing
information.

Store at 25°C (77°F); excursions permitted to 15° to 30°C (59° to 86°F).

Keep out of reach of children.

Dose mg

Distributed by:
Oceanside Pharmaceuticals, a division of
Bausch Health US, LLC
Bridgewater, NJ 08807 USA

Manufactured by:
DPT Laboratories, Ltd.
San Antonio, TX 78215 USA

© 2019 Bausch Health Companies Inc. or its affiliates

OCEANSIDE
PHARMACEUTICALS

PRINCIPAL DISPLAY PANEL - 20 mg Rectal Gel Label

NDC68682-655-20

Rx only

DIAZEPAM RECTAL GEL CIV

20 mgDelivery System

For Rectal Administration Only

LOT:

EXP:

Refer to package
insert for prescribing
information.

Store at 25°C (77°F); excursions permitted to 15° to 30°C (59° to 86°F).

Keep out of reach of children.

Dose mg

Distributed by:
Oceanside Pharmaceuticals, a division of
Bausch Health US, LLC
Bridgewater, NJ 08807 USA

Manufactured by:
DPT Laboratories, Ltd.
San Antonio, TX 78215 USA

© 2019 Bausch Health Companies Inc. or its affiliates

OCEANSIDE
PHARMACEUTICALS

Package/Label Display Panel – 2.5 mg Rectal Gel

NDC68682-650-20

Rx only

DIAZEPAM RECTAL GEL CIV

2.5 mg

For Rectal Administration Only
Refer to package insert for prescribing information.

Store at 25°C (77°F); excursions permitted to 15° to 30°C (59° to 86°F).
Keep out of reach of children.

Distributed by:
Oceanside Pharmaceuticals, a division of
Bausch Health US, LLC
Bridgewater, NJ 08807 USA

Manufactured by:
DPT Laboratories, Ltd.
San Antonio, TX 78215 USA

© 2019 Bausch Health Companies Inc. or its affiliates

LOT:

EXP:

OCEANSIDE
PHARMACEUTICALS